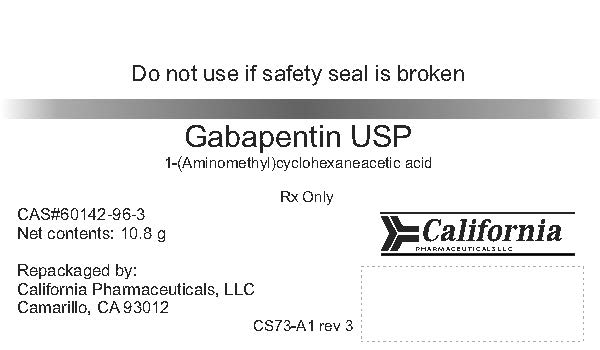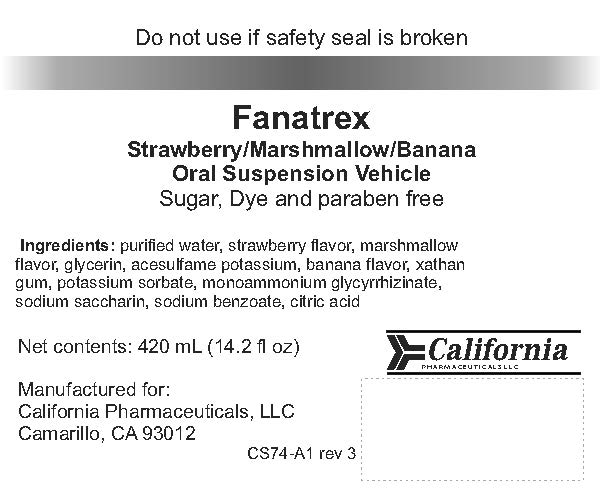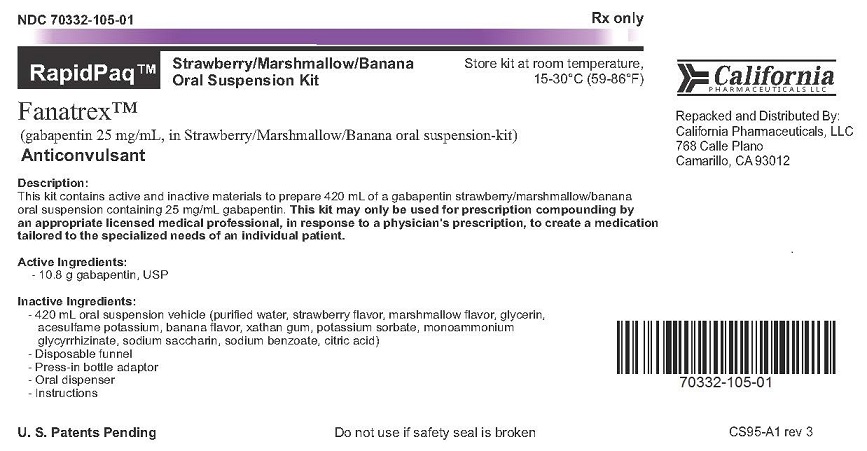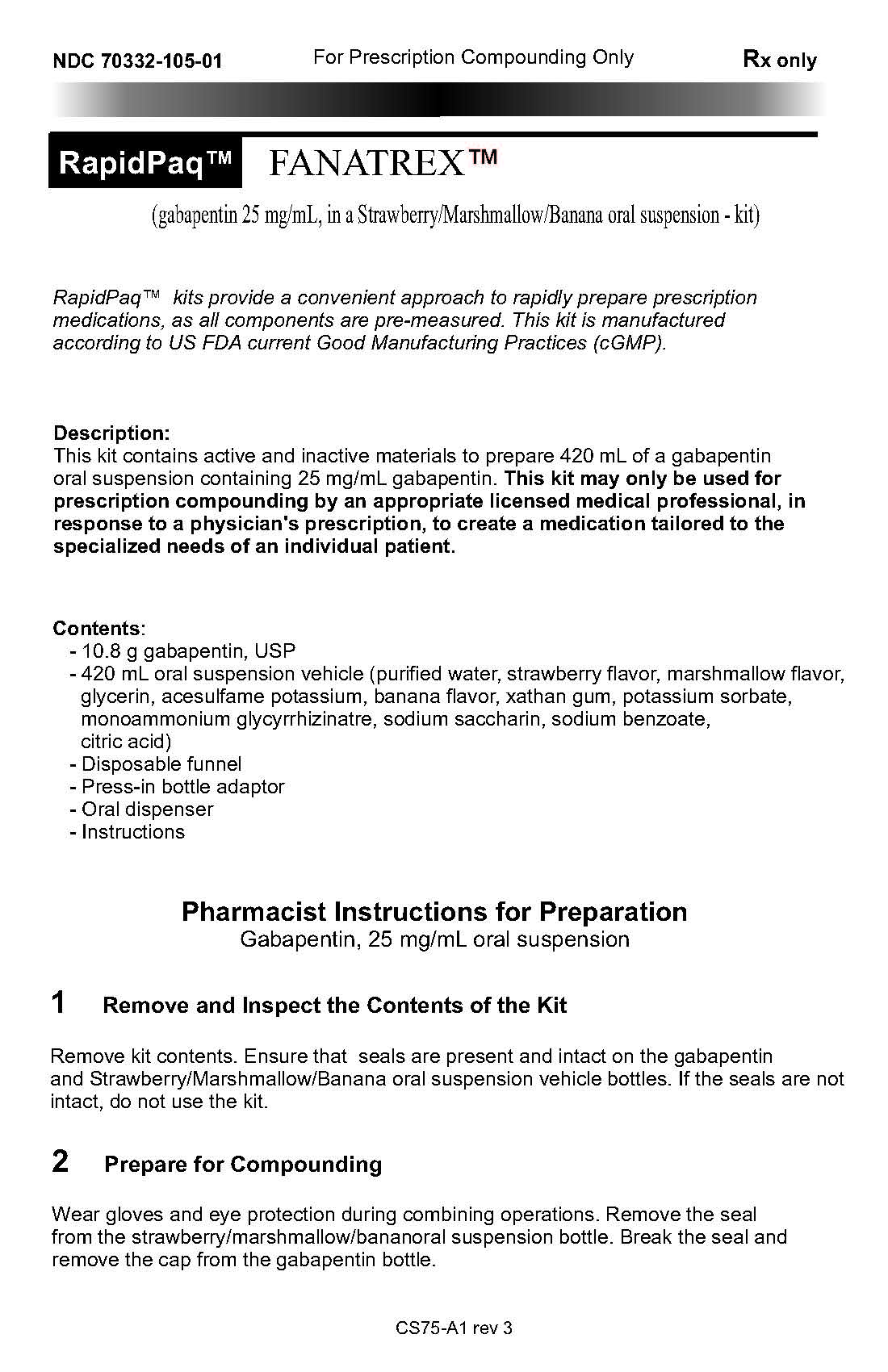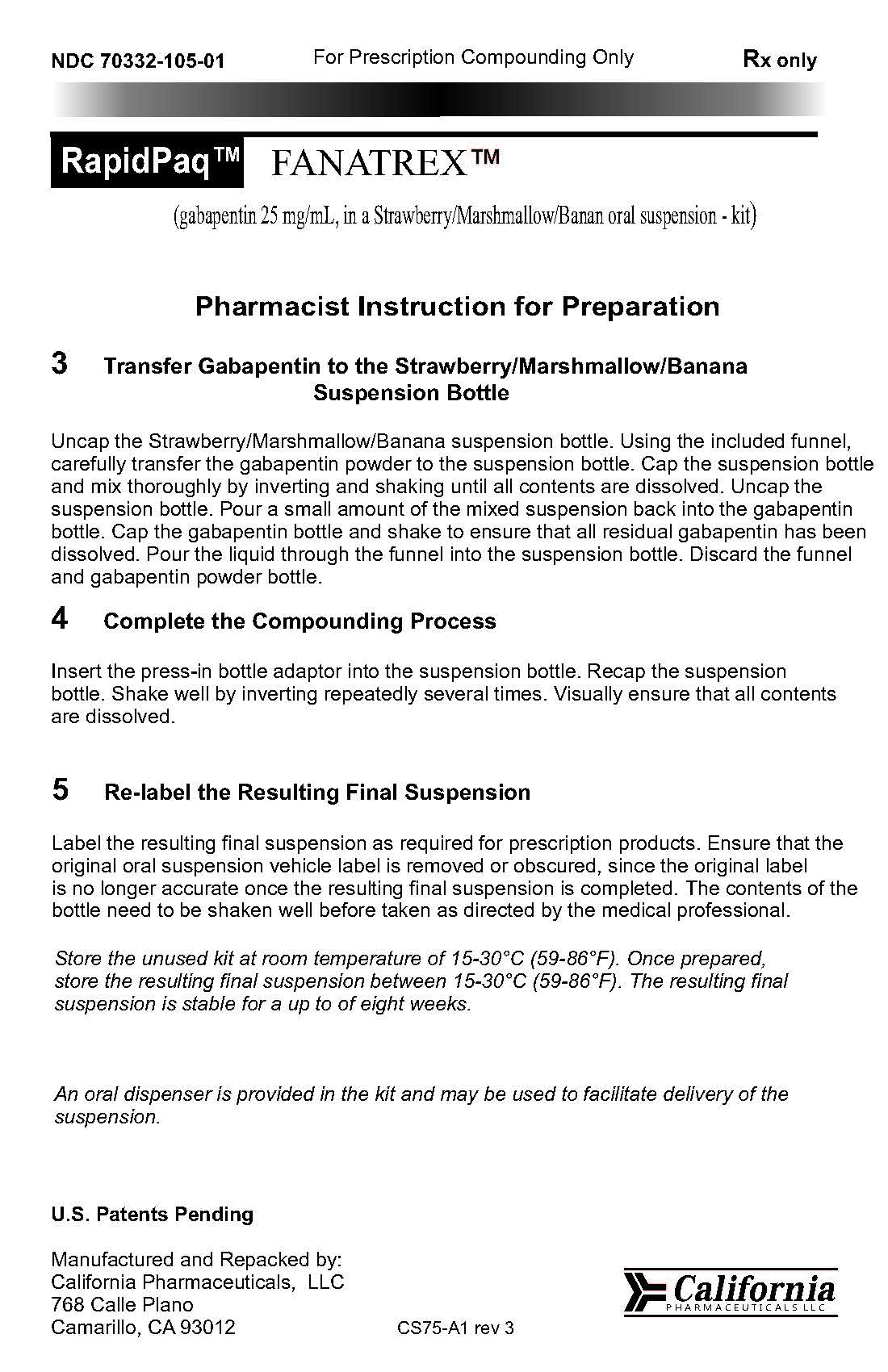 DRUG LABEL: Fanatrex
NDC: 70332-105 | Form: KIT | Route: ORAL
Manufacturer: California Pharmaceuticals, LLC
Category: prescription | Type: HUMAN PRESCRIPTION DRUG LABEL
Date: 20160107

ACTIVE INGREDIENTS: GABAPENTIN 10.8 g/10.8 g
INACTIVE INGREDIENTS: STEVIA LEAF; WATER; N-ACETYLGLUCOSAMINE; SODIUM PHOSPHATE, DIBASIC; GLYCYRRHIZIN, AMMONIATED; SACCHARIN SODIUM; BANANA; STRAWBERRY; ALTHAEA OFFICINALIS LEAF; GLYCERIN; ACESULFAME POTASSIUM; XANTHAN GUM; POTASSIUM SORBATE; SODIUM BENZOATE

Fanatrex